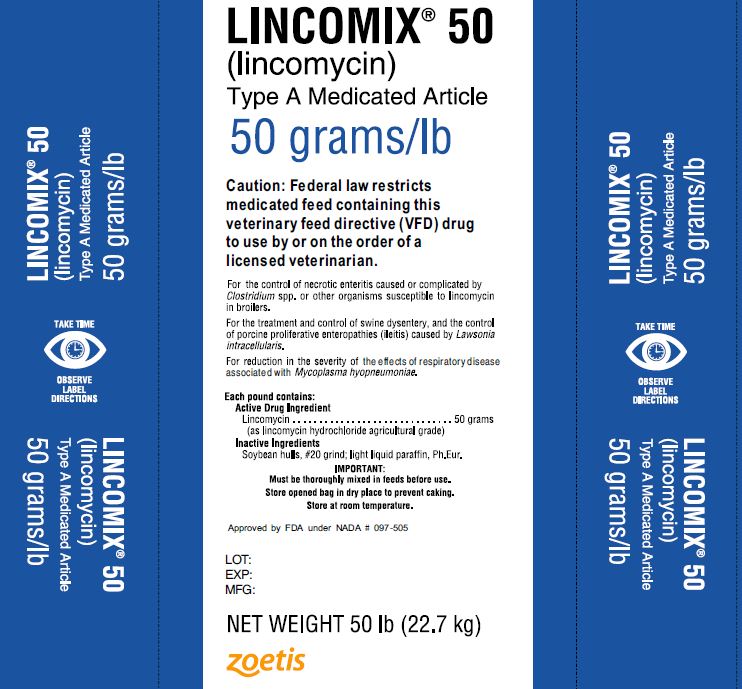 DRUG LABEL: Lincomix 50
NDC: 54771-1494 | Form: GRANULE
Manufacturer: Zoetis Inc.
Category: animal | Type: VFD TYPE A MEDICATED ARTICLE ANIMAL DRUG LABEL
Date: 20221208

ACTIVE INGREDIENTS: LINCOMYCIN HYDROCHLORIDE 50 g/0.453 kg

LINCOMIX® 50(lincomycin)

Type A Medicated Article

50 grams/lb

Caution: Federal law restricts medicated feed containing this veterinary feed directive (VFD) drug to use by or on the order of a licensed veterinarian.

For the control of necrotic enteritis caused or complicated by Clostridium spp. or other organisms susceptible to lincomycin in broilers.

For the treatment and control of swine dysentery, and the control of porcine proliferative enteropathies (ileitis) casued by Lawsonia intracellularis.

For reduction in the severity of the effects of respiratory disease associated with Mycoplasma hyopneumoniae.

Each pound contains:

Active Drug Ingredient

Lincomycin………………………………..50 grams

(as lincomycin hydrochloride agricultural grade)

Inactive Ingredients

Soybean hulls, #20 grind; light liquid paraffin, Ph.Eur.

IMPORTANT:

Must be thoroughly mixed in feeds before use.

Store opened bag in dry place to prevent caking.

Store at room temperature.

Approved by FDA under NADA # 097-505

BROILERS

For the control of necrotic enteritis caused or complicated by Clostridium spp. or other organisms susceptible to lincomycin in broilers.

DIRECTIONS FOR USE

For the control of necrotic enteritis:

LINCOMIX 50, 50 grams/lb, should be mixed into the complete feed supplied to broiler chickens so that the final feed contains 2 grams of lincomycin per ton of feed.

MIXING DIRECTIONS

Type C Medicated Feeds

Intermediate Premix; Amount of LINCOMIX 50 per 1000 lb; (454 kg) of Feed Ingredients | Complete Feed; Amount of Intermediate Premix to Provide 2 Grams; of lincomycin per ton of Type C Medicated Feed; lincomycin per ton of feed; 2 grams
20 lbs; 4 lbs; 2 lbs | 2 lbs; 10 lbs; 20 lbs

WARNING: When using LINCOMIX 50 in approved combinations with other drugs, follow the required withdrawal times for those drugs. No drug withdrawal period is required before slaughter of birds fed LINCOMIX 50 at the approved concentration (2 grams lincomycin per ton of feed).

CAUTION: Not for use in layers, breeders, or turkeys. (For additional Cautions, see below.)

SWINE

For the treatment and control of swine dysentery, and the control of porcine proliferative enteropathies (ileitis) caused by Lawsonia intracellularis. For reduction in the severity of the effects of respiratory disease associated with Mycoplasma hyopneumoniae.

DIRECTIONS FOR USE

For the treatment of swine dysentery, and the control of porcine proliferative enteropathies (ileitis) caused by Lawsonia intracellularis:

Feed 100 grams of lincomycin per ton of complete feed as the sole ration for three weeks, or until signs of disease (watery, mucoid or bloody stools) disappear.

For the treatment and control of swine dysentery, and the control of porcine proliferative enteropathies (ileitis) caused by Lawsonia intracellularis:

Feed 100 grams of lincomycin per ton of complete feed as the sole ration for three weeks, or until signs of disease (watery, mucoid or bloody stools) disappear, followed by 40 grams of lincomycin per ton.

For the control of swine dysentery and porcine proliferative enteropathies (ileitis) caused by Lawsonia intracellularis: Feed 40 grams of lincomycin per ton of complete feed as the sole ration. For use in animals or on premises with a history of swine dysentery, but where symptoms have not yet occurred.

For reduction in the severity of the effects of respiratory disease associated with Mycoplasma hyopneumoniae:

Feed 100-200 grams of lincomycin per ton of complete feed as the sole ration for 21 days.

MIXING DIRECTIONS

Type C Medicated Feeds

For treatment of swine dysentery, and the control of porcine proliferative enteropathies (ileitis) caused by Lawsonia intracellularis:

To make complete feed containing 100 grams of lincomycin, add 2 lbs of LINCOMIX 50 per ton.

For control of swine dysentery and porcine proliferative enteropathies (ileitis) caused by Lawsonia intracellularis:

To make complete feed containing 40 grams of lincomycin, add 0.8 lbs of LINCOMIX 50 per ton.

For reduction in the severity of the effects of respiratory disease associated with Mycoplasma hyopneumoniae:

To make complete feed containing 100- 200 grams of lincomycin, add 2-4 lbs of LINCOMIX 50 per ton.

Additional mixing directions to make complete feed containing 40, 100 or 200 grams of lincomycin per ton are provided below.

MIXING DIRECTIONS

Intermediate Premix; Amount of LINCOMIX 50 per 1000 lb; (454 kg) of Feed Ingredients | Complete Feed; Amount of Intermediate Premix to Provide Desired Grams of lincomycin per ton of Type C Medicated Feed; lincomycin per ton of feed
50 lbs; 40 lbs; 20 lbs | 40 grams 100 grams 200 grams; 16 lbs 40 lbs 80 lbs; 20 lbs 50 lbs 100 lbs; 40 lbs 100 lbs 200 lbs

WARNING: When using LINCOMIX 50 in approved combinations with other drugs, follow the required withdrawal times for those drugs. No drug withdrawal period is required before slaughter of swine fed LINCOMIX 50 at approved concentrations (40, 100 or 100-200 grams lincomycin per ton of feed).

NOT FOR HUMAN USE

CAUTION: Occasionally, swine fed lincomycin may within the first two days after the onset of treatment develop diarrhea and/or swelling of the anus. On rare occasions, some pigs may show reddening of the skin and irritable behavior. These conditions have been self-correcting within five to eight days without discontinuing the lincomycin treatment. The effects of lincomycin on swine reproductive performance, pregnancy, and lactation have not been determined.

Do not allow rabbits, hamsters, guinea pigs, horses, or ruminants access to feeds containing lincomycin. Ingestion by these species may result in severe gastrointestinal effects.

Good Manufacturing Practices Should Be Observed in Preparing Feeds Containing LINCOMIX 50.

This Includes Appropriate Clean-out Procedures to Avoid Cross-Contamination.

Restricted Drug (California) – Use Only as Directed

Distributed by:
Zoetis Inc.
Kalamazoo, MI 49007

501918

40027871

Made in China